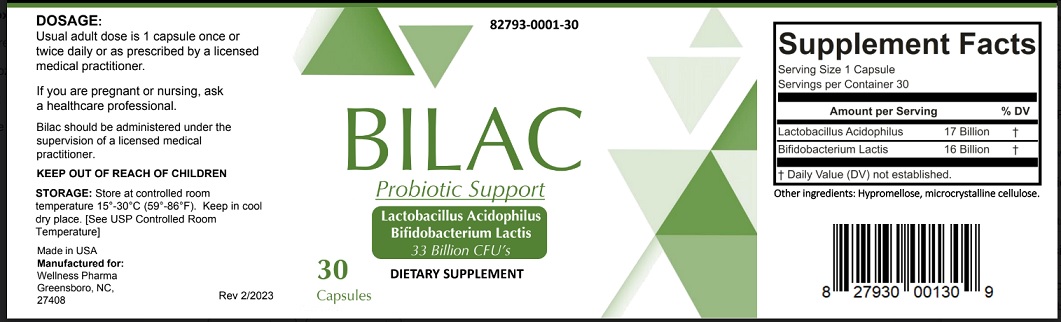 DRUG LABEL: Bilac
NDC: 82793-001 | Form: CAPSULE
Manufacturer: Wellness Pharma, LLC
Category: other | Type: DIETARY SUPPLEMENT
Date: 20230306

ACTIVE INGREDIENTS: LACTOBACILLUS ACIDOPHILUS 17000000000 [CFU]/1 1; BIFIDOBACTERIUM ANIMALIS LACTIS 16000000000 [CFU]/1 1
INACTIVE INGREDIENTS: MICROCRYSTALLINE CELLULOSE; HYPROMELLOSE, UNSPECIFIED

Statement of identity

Bilac is an orally administered prescription probiotic formulation for the clinical dietary management of suboptimal nutritional status in patients where advanced supplementation is required and nutritional supplementation in physiologically stressful conditions for maintenance of good health is needed.

Bilac should be administered under the supervision of a licensed medical practitioner.

Warning

This product is contraindicated in patients with a known hypersensitivity to any of the ingredients.

Bilac should be administered under the supervision of a licensed medical practitioner. Use with caution in patients that may have a medical condition, are pregnant, lactating, trying to conceive, under the age of 18, or taking medications.

KEEP THIS OUT OF THE REACH OF CHILDREN.

Dosage and administration

Usual adult dose is 1 capsule once or twice daily or as prescribed by a licensed medical practitioner.

Safe handling and warning

Store at controlled room temperature 15°-30°C (59°F-86°F). Keep in cool dry place. [See USP Controlled Room Temperature] Call your doctor about side effects. You may report side effects to FDA at 1-800-FDA-1088.